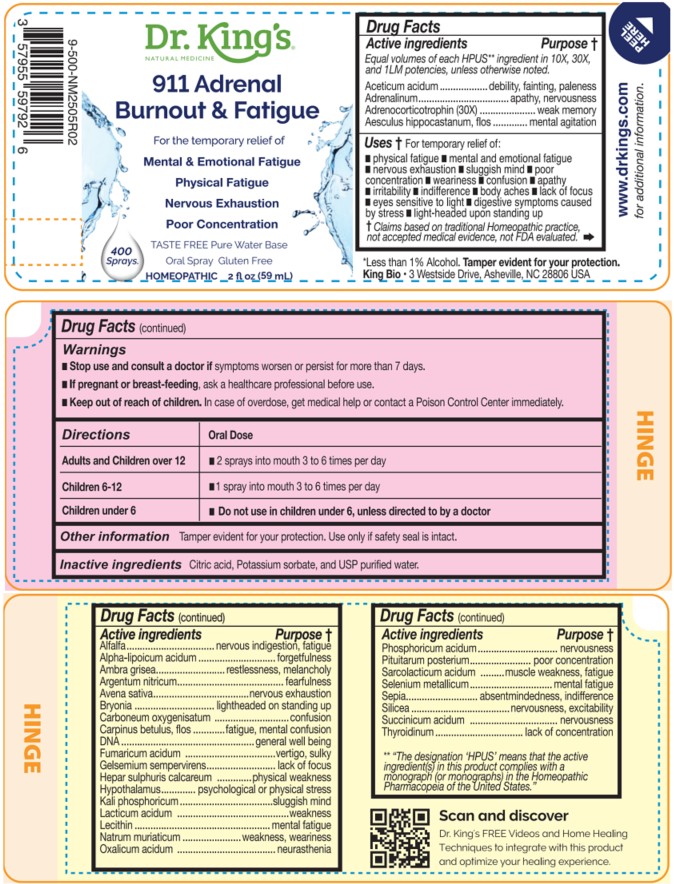 DRUG LABEL: 911 Adrenal Burnout and Fatigue
NDC: 57955-9994 | Form: LIQUID
Manufacturer: King Bio Inc.
Category: homeopathic | Type: HUMAN OTC DRUG LABEL
Date: 20260226

ACTIVE INGREDIENTS: ACETIC ACID 10 [hp_X]/59 mL; EPINEPHRINE 10 [hp_X]/59 mL; CORTICOTROPIN 30 [hp_X]/59 mL; AESCULUS HIPPOCASTANUM FLOWER 10 [hp_X]/59 mL; Alfalfa 10 [hp_X]/59 mL; ALPHA LIPOIC ACID 10 [hp_X]/59 mL; AMBERGRIS 10 [hp_X]/59 mL; SILVER NITRATE 10 [hp_X]/59 mL; AVENA SATIVA FLOWERING TOP 10 [hp_X]/59 mL; BRYONIA ALBA ROOT 10 [hp_X]/59 mL; CARBON MONOXIDE 10 [hp_X]/59 mL; CARPINUS BETULUS FLOWERING TOP 10 [hp_X]/59 mL; HERRING SPERM DNA 10 [hp_X]/59 mL; FUMARIC ACID 10 [hp_X]/59 mL; GELSEMIUM SEMPERVIRENS ROOT 10 [hp_X]/59 mL; CALCIUM SULFIDE 10 [hp_X]/59 mL; BOS TAURUS HYPOTHALAMUS 10 [hp_X]/59 mL; DIBASIC POTASSIUM PHOSPHATE 10 [hp_X]/59 mL; LACTIC ACID, DL- 10 [hp_X]/59 mL; EGG PHOSPHOLIPIDS 10 [hp_X]/59 mL; SODIUM CHLORIDE 10 [hp_X]/59 mL; OXALIC ACID DIHYDRATE 10 [hp_X]/59 mL; PHOSPHORIC ACID 10 [hp_X]/59 mL; SUS SCROFA PITUITARY GLAND, POSTERIOR 10 [hp_X]/59 mL; LACTIC ACID, L- 10 [hp_X]/59 mL; SELENIUM 10 [hp_X]/59 mL; SEPIA OFFICINALIS JUICE 10 [hp_X]/59 mL; SILICON DIOXIDE 10 [hp_X]/59 mL; SUCCINIC ACID 10 [hp_X]/59 mL; THYROID, UNSPECIFIED 10 [hp_X]/59 mL
INACTIVE INGREDIENTS: ANHYDROUS CITRIC ACID; POTASSIUM SORBATE; WATER

911 Adrenal Burnout and Fatigue

Active ingredients

Equal volumes of each HPUS** ingredient in 10X,
30X and 1LM potencies, unless otherwise noted.

Aceticum acidum, Adrenalinum, Adrenocorticotrophin (30X), Aesculus hippocastanum, flos, Alfalfa, Alpha-lipoicum acidum, Ambra grisea, Argentum nitricum, Avena sativa, Bryonia, Carboneum oxygenisatum, Carpinus betulus, flos, DNA, Fumaricum acidum, Gelsemium sempervirens, Hepar sulphuris calcareum, Hypothalamus, Kali phosphoricum, Lacticum acidum, Lecithin, Natrum muriaticum, Oxalicum acidum, Phosphoricum acidum, Pituitarum posterium, Sarcolacticum acidum, Selenium metallicum, Sepia, Silicea, Succinicum acidum and Thyroidinum.

** "The designation 'HPUS’ means that the active ingredient(s) in this product complies with a monograph (or Monographs) in the Homeopathic Pharmacopeia of the United States.″

INDICATIONS AND USAGE

Uses † for temporary relief of:

- physical fatigue
- mental and emotional fatigue
- nervous exhaustion
- sluggish mind
- poor concentration
- weariness
- confusion
- apathy
- irritability
- indifference
- body aches
- lack of focus
- eyes sensitive to light
- digestive symptoms caused by stress
- light-headed upon standing up

† Claims based on traditional Homeopathic practice, not accepted medical evidence, not
FDA evaluated.

Questions

911 Adrenal Burnout & Fatigue

Dr. King's Natural Medicine

Taste free, Pure Water Base

Oral Spray Gluten Free

HOMEOPATHIC 2 fl oz (59 mL)

*Less than 1% Alcohol Tamper evident for your protection.

King Bio • 3 Westside Drive, Asheville, NC 28806 USA

Scan and discover

Dr. King's FREE Videos and Home
Healing Techniques to integrate with
this product and optimize your
healing experience.

www.DrKings.com
for additional information.

Warnings

- Stop use and consult a doctor if symptoms worsen or persist for more than 7 days.
- If pregnant or breast-feeding, ask a healthcare professional before use.

- Keep out of reach of children. In case of overdose, get medical help or contact a Poison Control Center immediately.

DOSAGE AND ADMINISTRATION

Directions | Oral Dose
Adults and Children over 12 | - 2 sprays into mouth 3 to 6 times per day
Children 6-12 | - 1 spray into mouth 3 to 6 times per day
Children under 6 | - Do not use in children under 6, unless directed to by a doctor

Other information

Tamper evident for your protection.. Use only if safety seal is intact.

Inactive Ingredients

Citric Acid, Potassium Sorbate, and USP Purified Water.

PURPOSE

Equal volumes of each HPUS ** ingredient in 10X,
30X, and 1LM potencies, unless otherwise noted.

Active ingredients Purpose †

Aceticum acidum ........................debility, fainting, paleness
Adrenalinum.......................................apathy, nervousness
Adrenocorticotrophin (30X) ...........................weak memory
Aesculus hippocastanum, flos .....................mental agitation
Alfalfa......................................nervous indigestion, fatigue

Alpha-lipoicum acidum ...................................forgetfulness
Ambra grisea.................................restlessness, melancholy
Argentum nitricum.............................................fearfulness
Avena sativa..........................................nervous exhaustion
Bryonia .....................................lightheaded on standing up
Carboneum oxygenisatum .......confusion, cerebral congestion
Carpinus betulus, flos ....................fatigue, mental confusion
DNA ......................................................general well being
Fumaricum acidum ........................................vertigo, sulky
Gelsemium sempervirens..................................lack of focus
Hepar sulphuris calcareum .......................physical weakness
Hypothalamus....................... psychological or physical stress
Kali phosphoricum..........................................sluggish mind
Lacticum acidum .................................................weakness
Lecithin .......................................................mental fatigue
Natrum muriaticum ..............................weakness, weariness
Oxalicum acidum ............................................neurasthenia
Phosphoricum acidum.......................................nervousness

Pituitarum posterium.................................poor concentration
Sarcolacticum acidum .....................muscle weakness, fatigue
Selenium metallicum.......................................mental fatigue
Sepia.....................................absentmindedness, indifference
Silicea .............................................nervousness, excitability
Succinicum acidum ............................................nervousness
Thyroidinum...........................................lack of concentration

** "The designation 'HPUS’ means that the active ingredient(s) in this product complies with a monograph (or Monographs) in the Homeopathic Pharmacopeia of the United States.″

† Claims based on traditional Homeopathic practice, not accepted medical evidence, not
FDA evaluated.